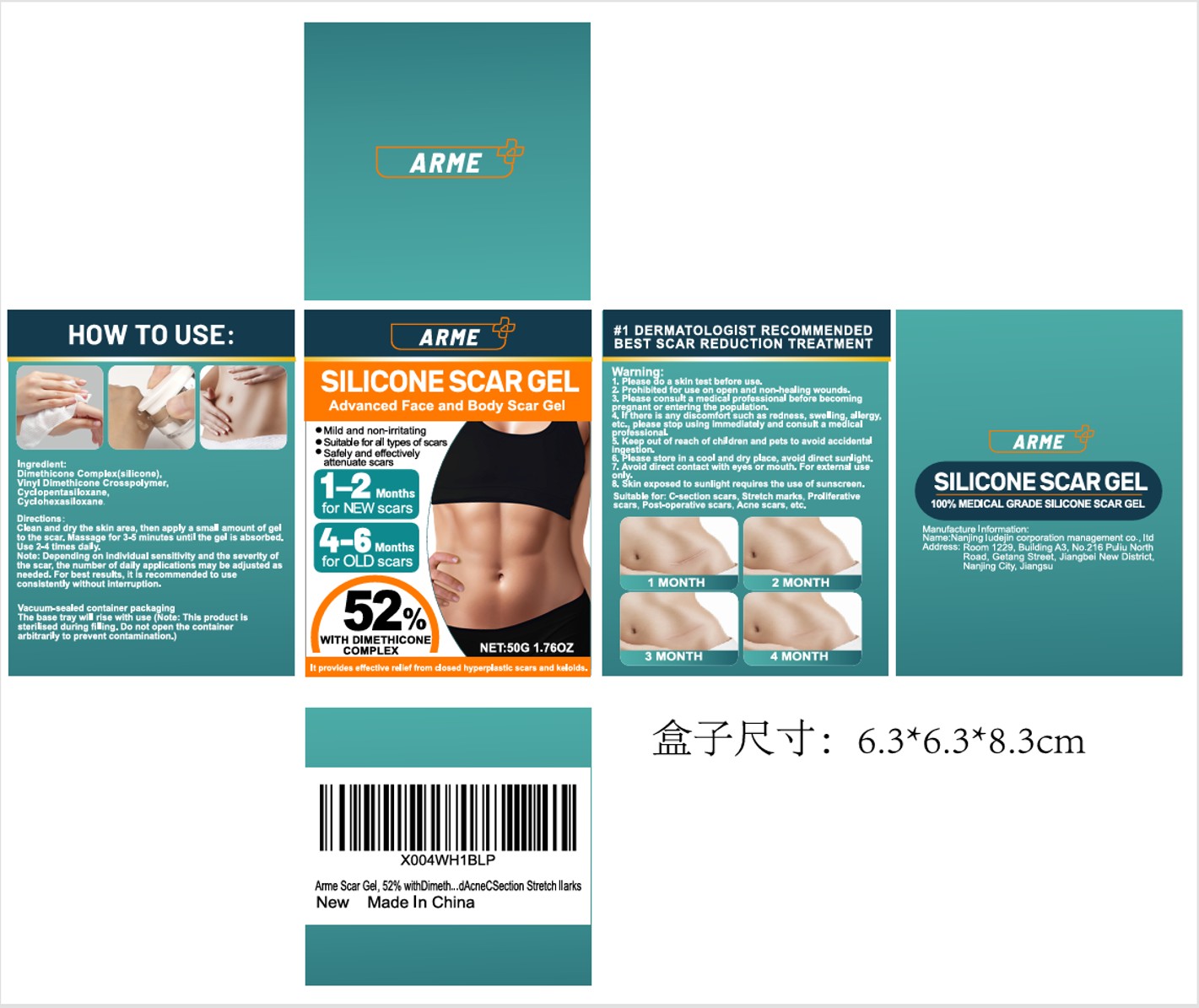 DRUG LABEL: Arme Scar Gel
NDC: 87165-002 | Form: GEL
Manufacturer: Nanjing Ludejin Corporation Management Co., Ltd
Category: otc | Type: HUMAN OTC DRUG LABEL
Date: 20251106

ACTIVE INGREDIENTS: DIMETHICONE 52 g/100 g
INACTIVE INGREDIENTS: CYCLOPENTASILOXANE; CYCLOHEXASILOXANE; VINYL DIMETHICONE/METHICONE SILSESQUIOXANE CROSSPOLYMER

87165-002 Arme Scar Gel

ACTIVE INGREDIENT

DIMETHICONE 52%

PURPOSE

Scar Gel

INDICATIONS AND USAGE

Mild and non-irritating
Suitabe for all types of scars
Safely and effectively attenuate scars

WARNINGS

For external use only

DO NOT USE

Prohibited foruse on open and non-healing wounds.
Please consult a medical professional before becoming pregnant or entering the population.

WHEN USING

Please do a skin test before use.
Avoid direct contact with eyes or mouth. For external useonly.
Skin exposed to sunlight requires the use of sunscreon.Suitable for:C-section scars,Stretch marks,Proliferativescars,Post-oporative scars, Acno scars, ctc.

STOP USE

If there is any discomfort such as rodnoss, sweling,allorgy,
etc.,please stop using immedlately and consult a medlcal Professional

KEEP OUT OF REACH OF CHILDREN

Keep out of reach of childron and pots to avoid accidontalIngestlon.

DOSAGE AND ADMINISTRATION

Clean and dry the skin area, then apply a small amount of gelto the scar, Massage for 3-5 minutes until the gol is absorbed.Use 2-4 times daly.
Note: Dopending on individual sensitivity and tho severity ofthe scar, the number of daily applications may be adjusted asneeded.Forbestresults,itls recommended to useconsistently without interruplion.

INACTIVE INGREDIENT

VINYL DIMETHICONE
Cyclopentasiloxane
Cyclohexasiloxane